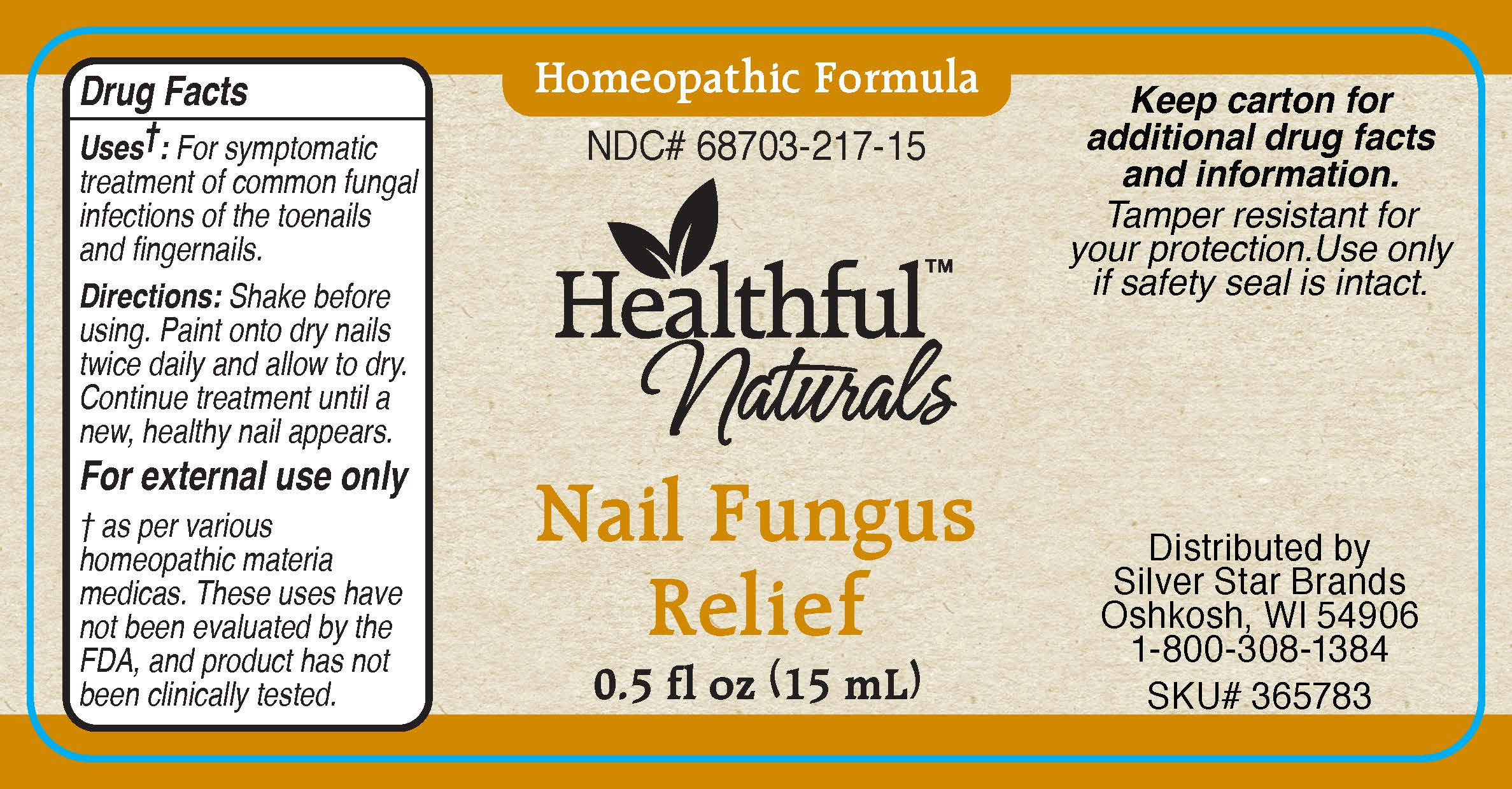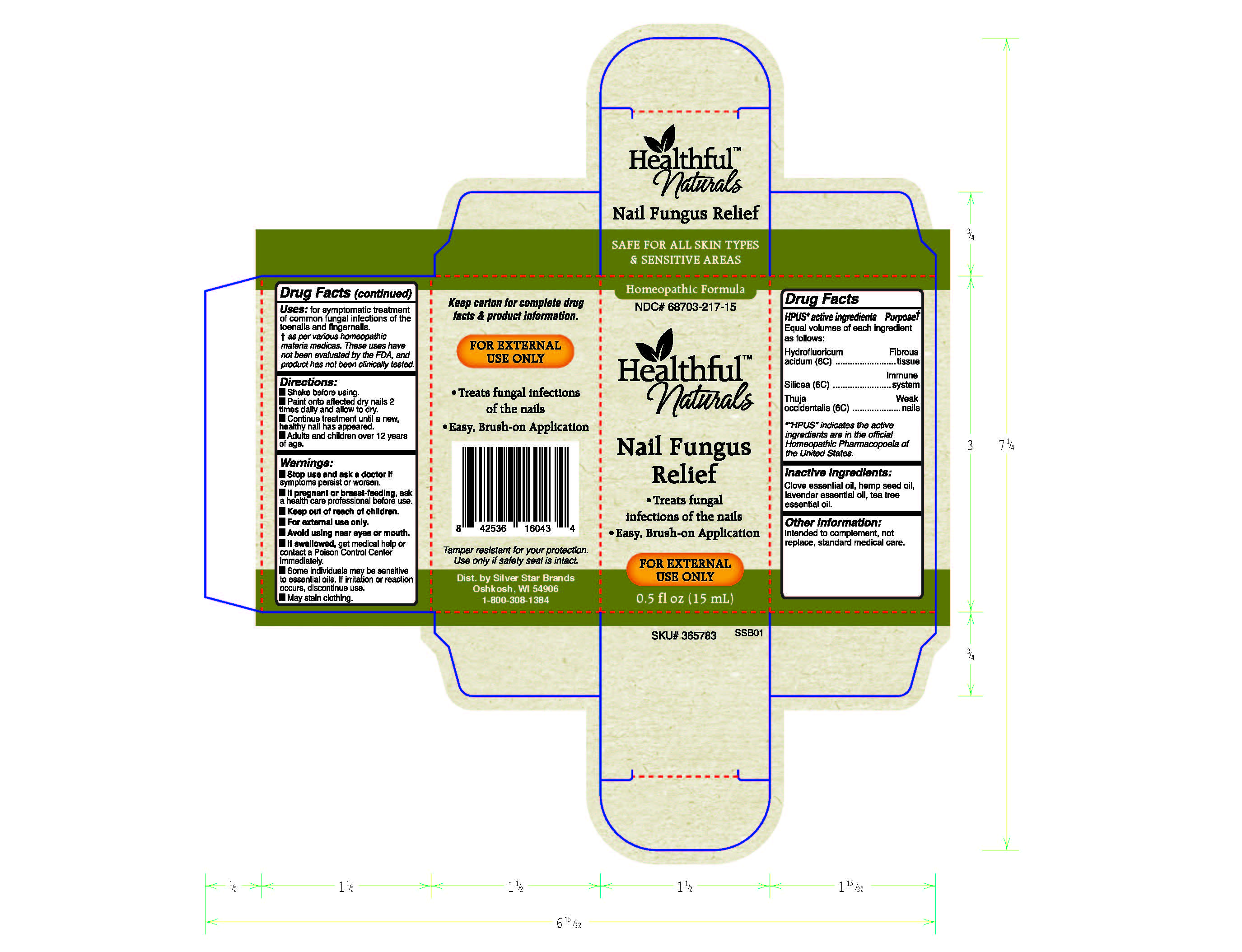 DRUG LABEL: Nail Fungus Relief
NDC: 68703-217 | Form: LIQUID
Manufacturer: Silver Star Brands
Category: homeopathic | Type: HUMAN OTC DRUG LABEL
Date: 20190228

ACTIVE INGREDIENTS: HYDROFLUORIC ACID 6 [hp_C]/15 mL; SILICON DIOXIDE 6 [hp_C]/15 mL; THUJA OCCIDENTALIS LEAFY TWIG 6 [hp_C]/15 mL
INACTIVE INGREDIENTS: TEA TREE OIL; LAVENDER OIL; CANNABIS SATIVA SEED OIL; CLOVE OIL

Healthful™ Naturals Nail Fungus Relief - 15 ml

HPUS* active ingredients - Equal volumes of each ingredient as follows: Hydrofluoricum acidum 6C, Silicea (6C), Thuja occidentalis (6C).

*"HPUS" indicates the active ingredients are in the official Homeopathic Pharmacopoeia of the United States.

Uses

Uses+: for symptomatic treatment of common fungal infections of the toenails and fingernails.

+As per various homeopathic materia medicas. These uses have not been evaluated by the FDA, and product has not been clinically tested.

Warnings

Warnings: Stop use and ask a doctor if symptoms persist or worsen.

If pregnant or breast-feeding, ask a health care professional before use.

Keep out of reach of children.

For external use only.

Avoid using near eyes or mouth.

If swallowed, get medical help or contact a Poison Control Center immediately.

Some individuals may be sensitive to essential oils. If irritation or reaction occurs, discontinue use.

May stain clothing.

Directions

Directions: Shake before using.

Paint onto affected dry nails 2 times daily and allow to dry.

Continue treatment until a new, healthy nail has appeared.

Adults and children over 12 years of age.

Other information:

Intended to complement, not replace, standard medical care.

Tamper resistant for your protection. Use only if safety seal is intact.

Inactive ingredients

Inactive ingredients: Clove essential oil, hempseed oil, lavender essential oil, tea tree essential oil.

Keep out of reach of children.

PREGNANCY OR BREAST FEEDING

If pregnant or breast-feeding, ask a health care professional before use.

HPUS* active ingredients Purpose+

Equal volumes of each ingredient as follows:

Hydrofluoricum acidum (6C).........................Fibrous tissue

Silicea (6C)...................................................Immune system

Thuja occidentalis (6C).................................Weak nails